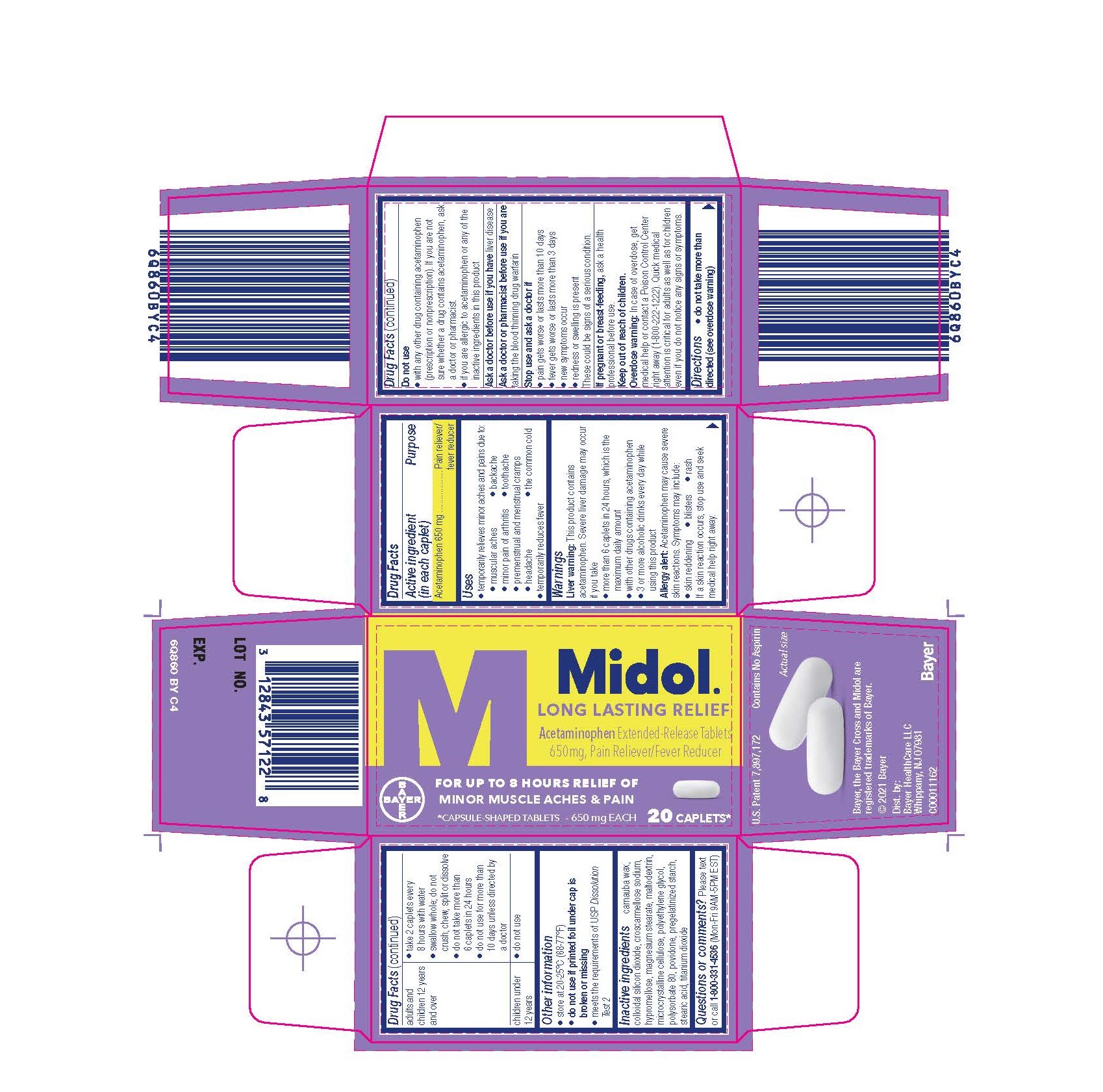 DRUG LABEL: Midol Long Lasting Relief
NDC: 0280-8090 | Form: TABLET, EXTENDED RELEASE
Manufacturer: Bayer HealthCare LLC.
Category: otc | Type: HUMAN OTC DRUG LABEL
Date: 20251204

ACTIVE INGREDIENTS: ACETAMINOPHEN 650 mg/1 1
INACTIVE INGREDIENTS: CARNAUBA WAX; HYPROMELLOSES; MAGNESIUM STEARATE; SILICON DIOXIDE; CROSCARMELLOSE SODIUM; MALTODEXTRIN; POLYETHYLENE GLYCOL, UNSPECIFIED; POLYSORBATE 80; POVIDONE; STEARIC ACID; MICROCRYSTALLINE CELLULOSE; STARCH, PREGELATINIZED CORN; TITANIUM DIOXIDE

Midol Long Lasting Relief

Drug Facts

Active ingredients (in each caplet)

Acetaminophen 650 mg

Purpose

Pain reliever/fever reducer

Uses

- Temporarily relieves minor aches and pains due

- muscular aches

- backache

- minor pain of athritis

- toothache

- premenstrual and mentrual cramps

- headache

- the common cold

- temporarily reduces fever

Warnings

Liver warning: The product contains acetaminophen. Severe liver damage may occur if you take

- more than 6 caplets in 24 hours, which is the maximum daily amount
- with other drugs containing acetaminophen
- 3 or more alcoholic drinks every day while using this product

Allergy Alert: Acetaminophen may cuse severe skin reactions.

Symptoms may include:

- skin reddening

- blisters

- rash

- If a skin reaction occurs, stop use and seek medical help right away.

Do not use

- with any other drug containing acetaminophen (prescription or nonprescription). If you are not sure whether a drug contains acetaminophen, ask a doctor or pharmacist. If you are not sure whether a drug contains acetaminophen, as a doctor or pharmacist.
- If you are allergic to acetaminophen or any of the inactive ingredients in this product.

Ask a doctor before use if you have liver disease

ASK DOCTOR/PHARMACIST

As a doctor or pharmacist before use if you are taking the blood thinning drug warfarin.

Stop use and ask a doctor if

- pain gets worse or lasts more than 10 days
- fever gets worse or lasts more than 3 days
- new symptoms occur
- redness or swelling is present

These could be signs of a serious condition

PREGNANCY OR BREAST FEEDING

If pregnant or breast-feeding, ask a health professional before use.

Keep out of reach of children.

Overdose warning: In case of overdose, get medical help or contact a Poison Control Center right away (1-800-222-1222). Quick medical attention is critical for adults as well as for children even if you do not notice any signs or symptoms.

Directions

- do not take more than directed (see overdose warning)

adults and children 12 years and over | - take 2 caplets every 8 hours with water - swallow whole; do not crush, chew, split or dissolve - do not take more than 6 caplets in 24 hours - do not use for more than 10 days unless directed by a doctor
children under 12 years | - do not use

Other information

- store at 20-25° (68-77°F). Avoid excessive heat 40°C (104°F).
- do not use if printedfoil under cap is broken or missing

INACTIVE INGREDIENT

Inactive ingredients carnauba wax, colloidal silicon dioxide, croscarmellose sodium, hypromellose, magnesium stearate, maltodextrin, microcrystalline cellulose, polyethylene glycolpolysorbate 80, povidone, pregelatinized starch, stearic acid, titanium dioxide

Questions or comments? 1-800-331-4536